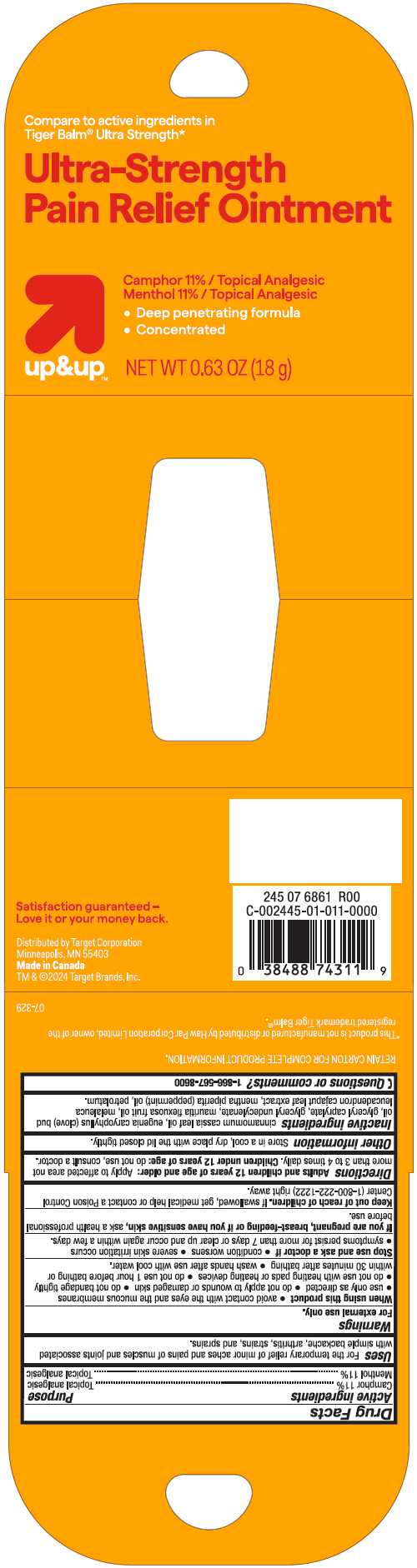 DRUG LABEL: Ultra-Strength Pain Relief
NDC: 82442-311 | Form: OINTMENT
Manufacturer: TARGET CORPORATION
Category: otc | Type: HUMAN OTC DRUG LABEL
Date: 20241030

ACTIVE INGREDIENTS: CAMPHOR (SYNTHETIC) 110 mg/1 g; MENTHOL, UNSPECIFIED FORM 110 mg/1 g
INACTIVE INGREDIENTS: CHINESE CINNAMON LEAF OIL; CLOVE OIL; GLYCERYL MONOCAPRYLATE; GLYCERYL 1-UNDECYLENATE; Mauritia Flexuosa Fruit Oil; PEPPERMINT OIL; Petrolatum

Ultra-Strength Pain Relief Ointment
Topical Analgesic

Drug Facts

ACTIVE INGREDIENT

Active ingredient | Purpose
Camphor 11% | Topical analgesic
Menthol 11% | Topical analgesic

Uses

For the temporary relief of minor aches and pains of muscles and joints associated with simple backache, arthritis, strains, and sprains.

Warnings

For external use only

When using this product

- avoid contact with the eyes and the mucous membranes
- use only as directed
- do not apply to wounds or damaged skin
- do not bandage tightly
- do not use with heating pads or heating devices
- do not use 1 hour before bathing or within 30 minutes after bathing
- wash hands after use with cool water.

Stop use and ask a doctor if

- condition worsens
- severe skin irritation occurs
- symptoms persist for more than 7 days or clear up and occur again within a few days.

PREGNANCY OR BREAST FEEDING

If you are pregnant, or breast-feeding or if you have sensitive skin, ask a health professional before use.

Keep out of reach of children. If swallowed, get medical help or contact a Poison Control Center (1-800-222-1222) right away.

Directions

Adults and children 12 years of age and older: Apply to affected area not more than 3 to 4 times daily. Children under 12 years of age: do not use, consult a doctor.

Other information

store in a cool dry place with the lid closed tightly.

Inactive ingredients

Cinnamomum Cassia Leaf Oil, Eugenia Caryophyllus (Clove) Bud Oil, Glyceryl Caprylate, Glyceryl Undecylenate, Mauritia Flexuosa Fruit Oil, Melaleuca Leucadendron Cajaput Leaf Extract, Mentha Piperita (Peppermint) Oil, Petrolatum

Questions or comments?

1-866-567-8600

Distributed by Target Corporation
Minneapolis, MN 55403

PRINCIPAL DISPLAY PANEL - 18 g Jar Carton

Compare to active ingredients in
Tiger Balm® Ultra Strength*

Ultra-Strength
Pain Relief Ointment

Camphor 11% / Topical Analgesic
Menthol 11% / Topical Analgesic

- Deep penetrating formula
- Concentrated

up&up™
NET WT 0.63 OZ (18 g)